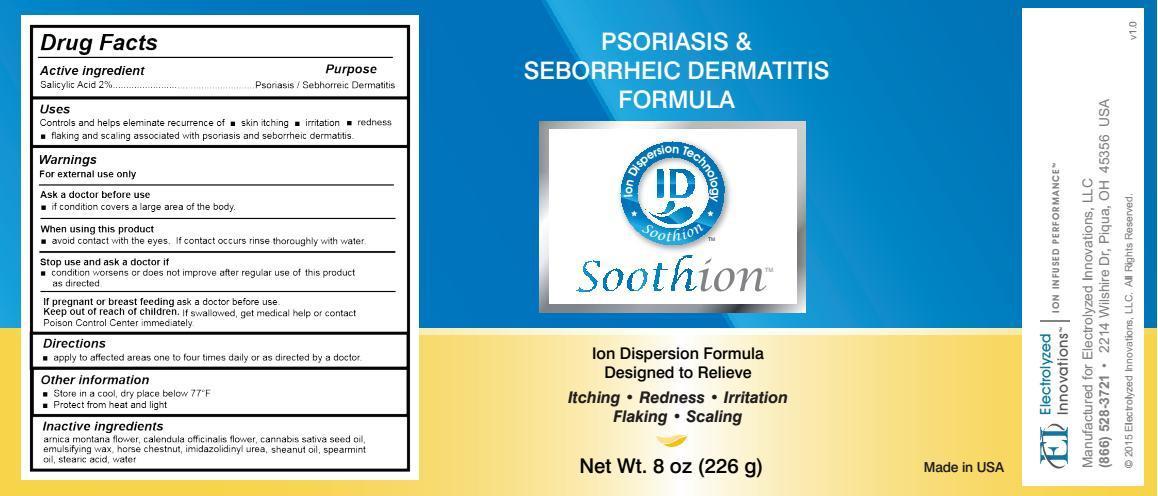 DRUG LABEL: Soothion Psoriasis and Seborrheic Dermatitis Formula
NDC: 69031-004 | Form: LOTION
Manufacturer: Electrolyzed Innovations, LLC
Category: otc | Type: HUMAN OTC DRUG LABEL
Date: 20191223

ACTIVE INGREDIENTS: SALICYLIC ACID 2 g/100 g
INACTIVE INGREDIENTS: ARNICA MONTANA FLOWER; CALENDULA OFFICINALIS FLOWER; CANNABIS SATIVA SEED OIL; HORSE CHESTNUT; IMIDUREA; SHEANUT OIL; SPEARMINT OIL; STEARIC ACID; WATER

Drug Facts

Active ingredient

Salicylic Acid 2%

Purpose

Psoriasis / Seborrheic Dermatitis

Uses

Controls and helps eliminate recurrence of:

- skin itching
- irritation
- redness
- flaking and scaling associated with psoriasis and seborrheic dermatitis.

Warnings

For external use only.

Ask a doctor before use

- if condition covers a large area of the body.

When using this product

- avoid contact with the eyes. If contact occurs rinse eyes thoroughly with water.

Stop use and ask a doctor if

- condition worsens or does not improve after regular use of this product as directed.

PREGNANCY OR BREAST FEEDING

If pregnant or breast feeding ask a doctor before use.

Keep out of reach of children. If swallowed, get medical help or contact Poison Control Center immediately.

Directions

- apply to affected areas one to four times daily or as directed by a doctor.

Other information

- Store in a cool, dry place below 77°F
- Protect from heat and light

Inactive ingredients

arnica montana flower, calendula officinalis flower, cannabis sativa seed oil, emulsifying wax, horse chestnut, imidazolidinyl urea, sheanut oil, spearmint oil, stearic acid, water

DESCRIPTION

Manufactured for Electrolyzed Innovations, LLC
(866) 528-3721 2214 Wilshire Dr, Piqua, OH 45356 USA

Principal Display Panel

Psoriasis and Seborrheic Dermatitis Formula

Soothion

Ion Dispersion Formula Designed to Relieve

- Itching
- Redness
- Irritation
- Flaking
- Scaling

Net Wt. 8 oz (226 g) Made in USA